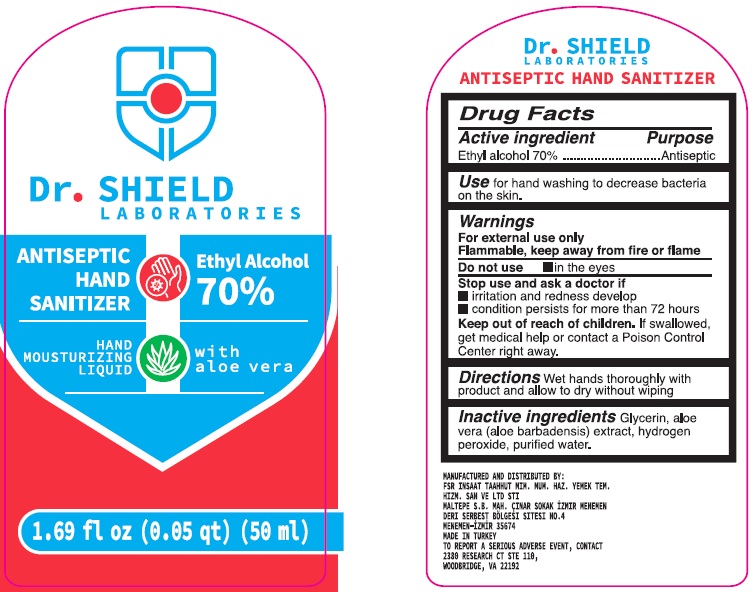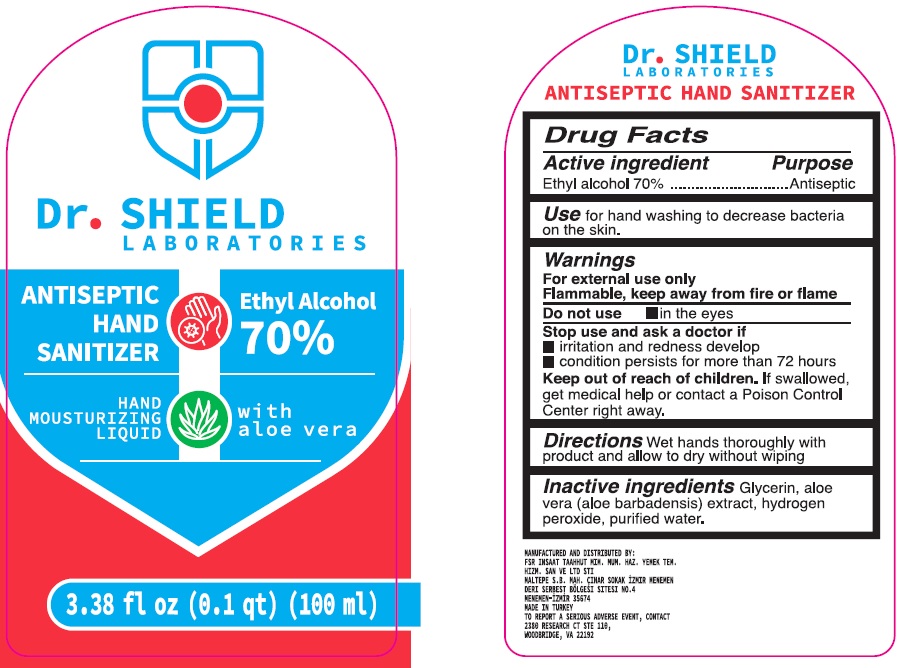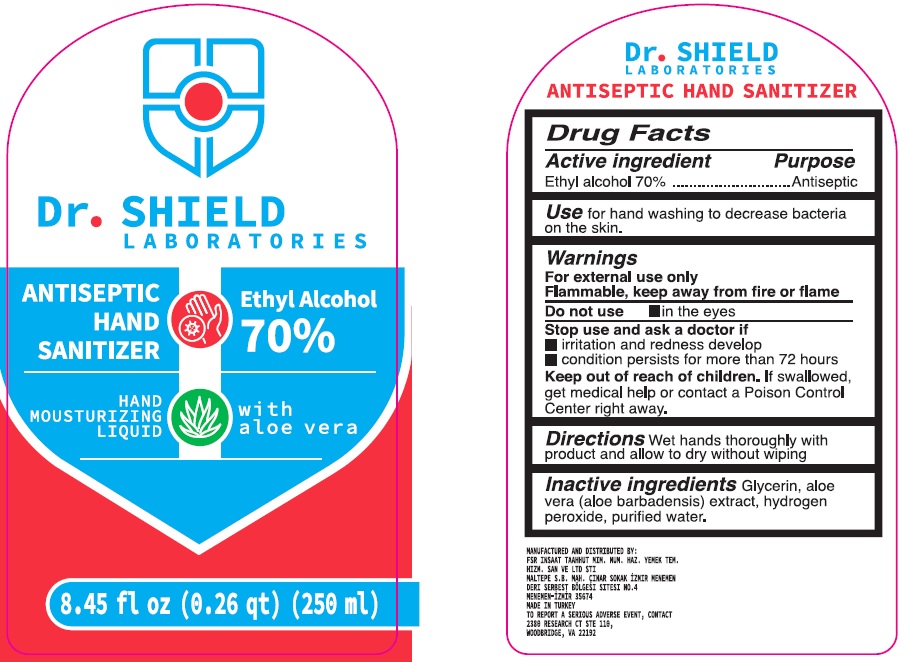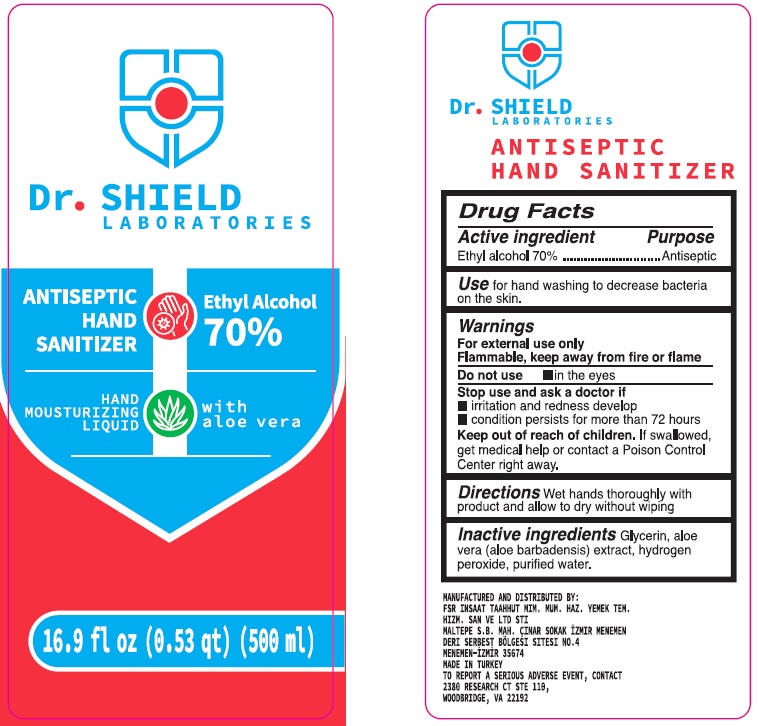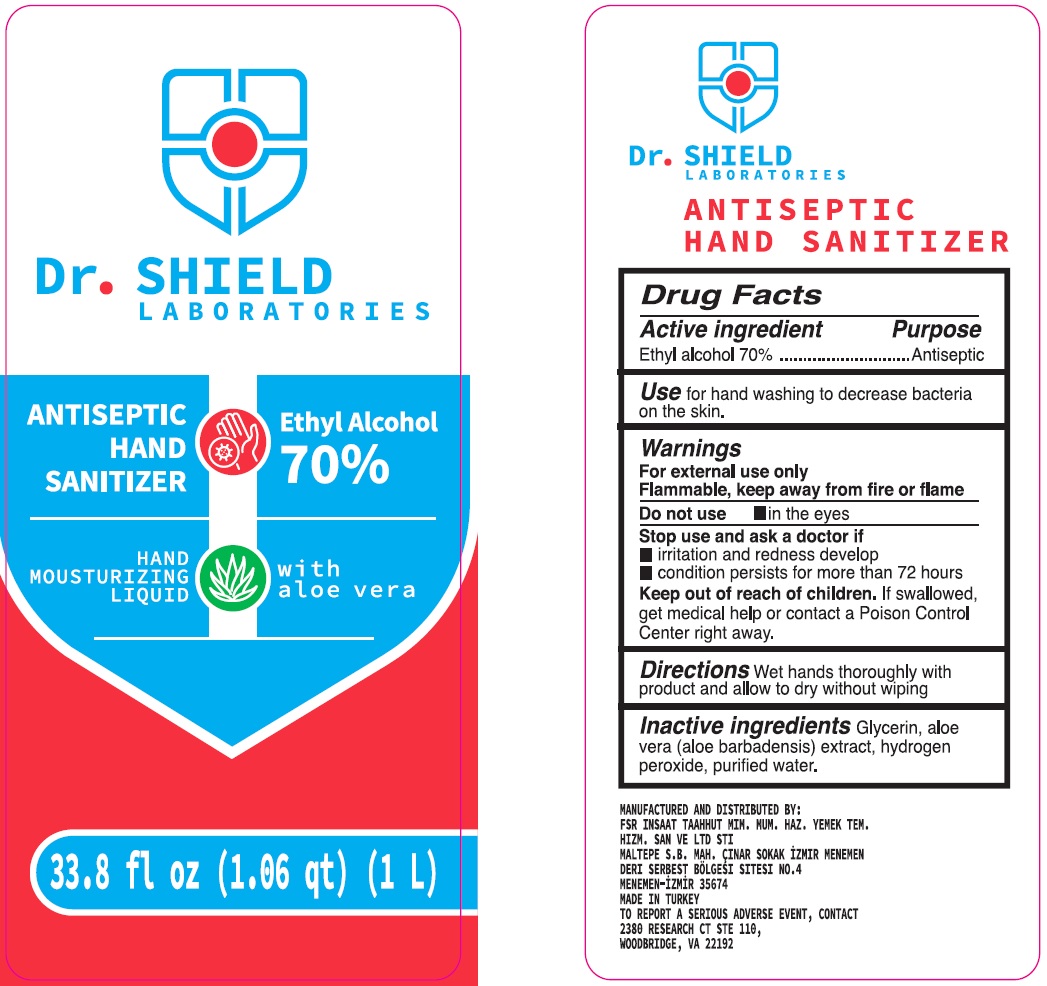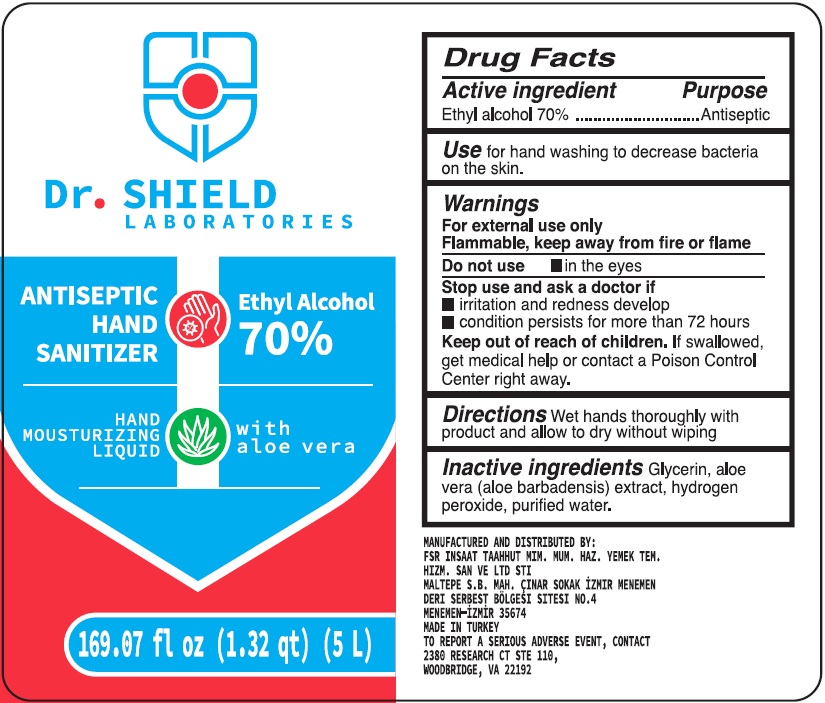 DRUG LABEL: Dr. Shield Laboratories Antiseptic Hand Sanitizer
NDC: 81262-001 | Form: LIQUID
Manufacturer: FSR INS TAAH MIM MUH HAZIR YEMEK TEM HIZLERI SAN VE TIC LTD STI IZMIR SERBEST BOLGE SUBESI
Category: otc | Type: HUMAN OTC DRUG LABEL
Date: 20201216

ACTIVE INGREDIENTS: ALCOHOL 0.7 mL/1 mL
INACTIVE INGREDIENTS: GLYCERIN; ALOE VERA LEAF; HYDROGEN PEROXIDE; WATER

Dr. Shield Laboratories Antiseptic Hand Sanitizer

Active ingredient

Ethyl alcohol 70%

Purpose

Antiseptic

Use

for hand washing to decrease bacteria on the skin.

Warnings

For external use only

Flammable, keep away from fire or flame

Do not use

- in the eyes

Stop use and ask a doctor if

- irritation and redness develop
- condition persists for more than 72 hours

Keep out of reach of children.

If swallowed, get medical help or contact a Poison Control Center right away.

Directions

Wet hands thoroughly with product and allow to dry without wiping

Inactive ingredients

Glycerin, aloe vera (aloe barbadensis) extract, hydrogen peroxide, purified water.